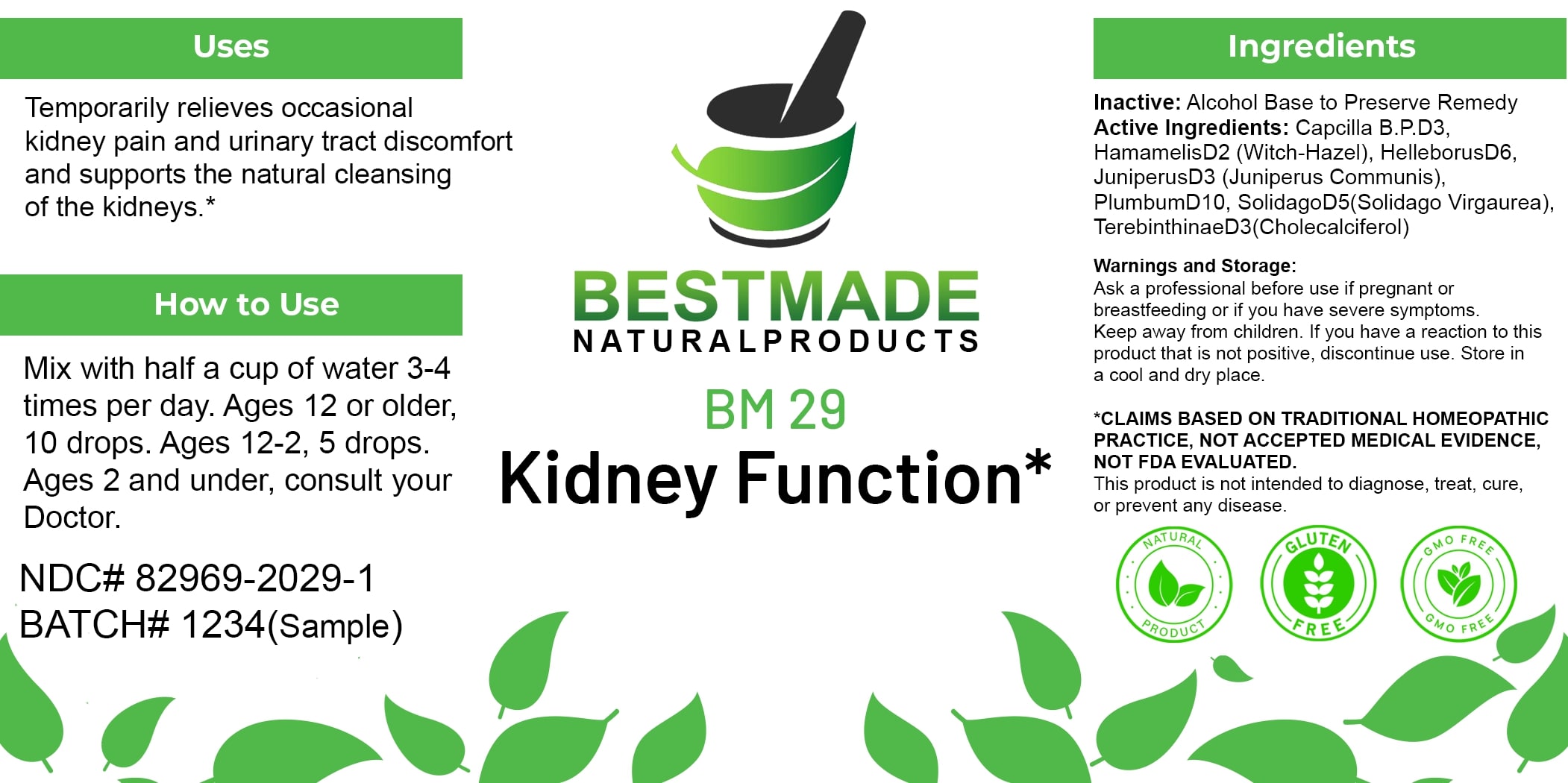 DRUG LABEL: Bestmade Natural Products BM29
NDC: 82969-2029 | Form: LIQUID
Manufacturer: Bestmade Natural Products
Category: homeopathic | Type: HUMAN OTC DRUG LABEL
Date: 20250123

ACTIVE INGREDIENTS: JUNIPER BERRY 30 [hp_C]/30 [hp_C]; LEAD 30 [hp_C]/30 [hp_C]; HELLEBORUS NIGER ROOT 30 [hp_C]/30 [hp_C]; HAMAMELIS VIRGINIANA ROOT BARK/STEM BARK 30 [hp_C]/30 [hp_C]; CAPSICUM 30 [hp_C]/30 [hp_C]; SOLIDAGO VIRGAUREA FLOWERING TOP 30 [hp_C]/30 [hp_C]; TURPENTINE OIL 30 [hp_C]/30 [hp_C]
INACTIVE INGREDIENTS: ALCOHOL 30 [hp_C]/30 [hp_C]

BM29

DOSAGE AND ADMINISTRATION

How to Use

Mix with half a cup of water 3-4 times per day. Ages 12 or older, 10 drops. Ages 12-2, 5 drops. Ages 2 and under, consult your Doctor.

INACTIVE INGREDIENT

Ingredients

Inactive: Alcohol Base to Preserve Remedy

Uses

Temporarily relieves occasional kidney pain and urinary tract discomfort and supports the natural cleansing of the kidneys.*

*CLAIMS BASED ON TRADITIONAL HOMEOPATHIC PRACTICE, NOT ACCEPTED MEDICAL EVIDENCE. NOT FDA EVALUATED.

This product is not intended to diagnose, treat, cure, or prevent any disease.

ACTIVE INGREDIENT

Active Ingredients: Capcilla B.P.D3, Hamamelis D2 (Witch-Hazel), Helleborus D6, Juniperus D3 (Juniperus Communis), Plumbum D10, Solidago D5 (Solidago Virgaurea), Terebinthinae D3 (Cholecalciferol)

KEEP OUT OF REACH OF CHILDREN

Warnings and Storage:

Ask a professional before use if pregnant or breastfeeding or if you have severe symptoms. Keep away from children. If you have a reaction to this product that is not positive, discontinue use. Store in a cool and dry place.

Uses

Temporarily relieves occasional kidney pain and urinary tract discomfort and supports the natural cleansing of the kidneys.*

*CLAIMS BASED ON TRADITIONAL HOMEOPATHIC PRACTICE, NOT ACCEPTED MEDICAL EVIDENCE. NOT FDA EVALUATED.

This product is not intended to diagnose, treat, cure, or prevent any disease.

Warnings and Storage:

Ask a professional before use if pregnant or breastfeeding or if you have severe symptoms. Keep away from children. If you have a reaction to this product that is not positive, discontinue use. Store in a cool and dry place.

*CLAIMS BASED ON TRADITIONAL HOMEOPATHIC PRACTICE, NOT ACCEPTED MEDICAL EVIDENCE. NOT FDA EVALUATED.

This product is not intended to diagnose, treat, cure, or prevent any disease.

Entire package label